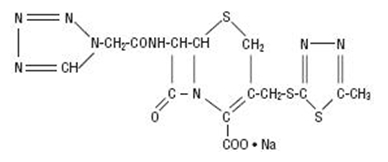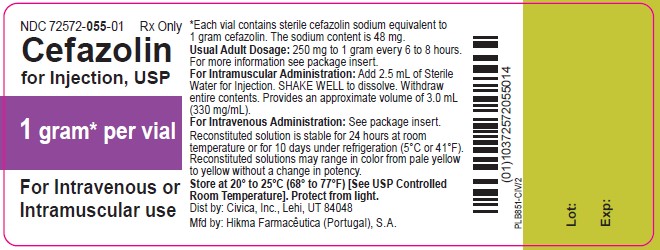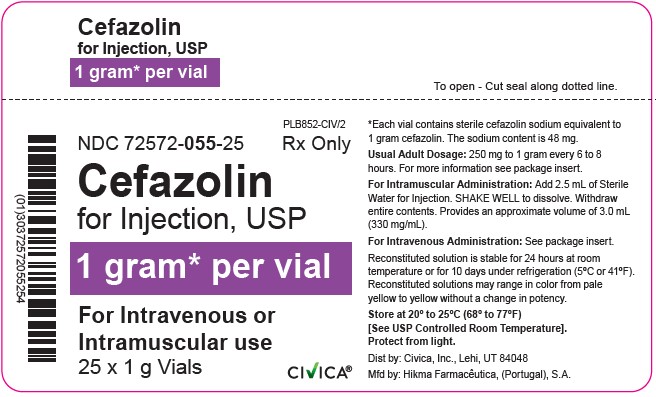 DRUG LABEL: Cefazolin
NDC: 72572-055 | Form: INJECTION, POWDER, FOR SOLUTION
Manufacturer: Civica, Inc.
Category: prescription | Type: HUMAN PRESCRIPTION DRUG LABEL
Date: 20260129

ACTIVE INGREDIENTS: CEFAZOLIN SODIUM 1 g/1 1

CEFAZOLIN FOR INJECTION, USP

Rx Only

To reduce the development of drug-resistant bacteria and maintain the effectiveness of Cefazolin for Injection and other antibacterial drugs, Cefazolin for Injection should be used only to treat or prevent infections that are proven or strongly suspected to be caused by bacteria.

DESCRIPTION

Cefazolin for Injection, USP is a semi-synthetic cephalosporin for parenteral administration. It is the sodium salt of 3-{[(5-methyl-1,3,4-thiadiazol-2-yl)thio]-methyl}-8-oxo-7-[2-(1H-tetrazol-1-yl) acetamido]-5-thia-1-azabicyclo [4.2.0]oct-2-ene-2-carboxylic acid. The molecular formula is C14H13N8NaO4S3 and molecular weight is 476.49.

Structural Formula:

Each vial contains 48 mg of sodium/1 gram of cefazolin sodium.

Cefazolin for Injection, USP is white to off-white crystalline powder, supplied in vials equivalent to 1 gram of cefazolin.

CLINICAL PHARMACOLOGY

After intramuscular administration of Cefazolin for Injection to normal volunteers, the mean serum concentrations were 37 mcg/mL at 1 hour and 3 mcg/mL at 8 hours following a 500 mg dose, and 64 mcg/mL at 1 hour and 7 mcg/mL at 8 hours following a 1 gram dose.

Studies have shown that following intravenous administration of Cefazolin for Injection to normal volunteers, mean serum concentrations peaked at approximately 185 mcg/mL and were approximately 4 mcg/mL at 8 hours for a 1 gram dose.

The serum half-life for Cefazolin for Injection is approximately 1.8 hours following IV administration and approximately 2 hours following IM administration.

In a study (using normal volunteers) of constant intravenous infusion with dosages of 3.5 mg/kg for 1 hour (approximately 250 mg) and 1.5 mg/kg the next 2 hours (approximately 100 mg), Cefazolin for Injection produced a steady serum level at the third hour of approximately 28 mcg/mL.

Studies in patients hospitalized with infections indicate that Cefazolin for Injection produces mean peak serum levels approximately equivalent to those seen in normal volunteers.

Bile levels in patients without obstructive biliary disease can reach or exceed serum levels by up to five times; however, in patients with obstructive biliary disease, bile levels of Cefazolin for Injection are considerably lower than serum levels (< 1 mcg/mL).

In synovial fluid, the level of Cefazolin for Injection becomes comparable to that reached in serum at about 4 hours after drug administration. Studies of cord blood show prompt transfer of Cefazolin for Injection across the placenta. Cefazolin for Injection is present in very low concentrations in the milk of nursing mothers.

Cefazolin for Injection is excreted unchanged in the urine. In the first 6 hours approximately 60% of the drug is excreted in the urine and this increases to 70% to 80% within 24 hours. Cefazolin for Injection achieves peak urine concentrations of approximately 2,400 mcg/mL and 4,000 mcg/mL respectively following 500 mg and 1 gram intramuscular doses.

In patients undergoing peritoneal dialysis (2 L/hr.), Cefazolin for Injection produced mean serum levels of approximately 10 and 30 mcg/mL after 24 hours’ instillation of a dialyzing solution containing 50 mg/L and 150 mg/L, respectively. Mean peak levels were 29 mcg/mL (range 13 to 44 mcg/mL) with 50 mg/L (3 patients), and 72 mcg/mL (range 26 to 142 mcg/mL) with 150 mg/L (6 patients). Intraperitoneal administration of Cefazolin for Injection is usually well tolerated.

Controlled studies on adult normal volunteers, receiving 1 gram 4 times a day for 10 days, monitoring CBC, SGOT, SGPT, bilirubin, alkaline phosphatase, BUN, creatinine and urinalysis, indicated no clinically significant changes attributed to Cefazolin for Injection.

Microbiology

Mechanism of Action

Cefazolin is a bactericidal agent that acts by inhibition of bacterial cell wall synthesis.

Resistance

Predominant mechanisms of bacterial resistance to cephalosporins include the presence of extended-spectrum beta-lactamases and enzymatic hydrolysis.

Antimicrobial Activity

Cefazolin has been shown to be active against most isolates of the following microorganisms, both in vitro and in clinical infections as described in the INDICATIONS AND USAGE (1) section:

Gram-Positive Bacteria:
Staphylococcus aureus
Staphylococcus epidermidis
Streptococcus agalactiae
Streptococcus pneumoniae
Streptococcus pyogenes

Methicillin-resistant staphylococci are uniformly resistant to cefazolin.

Gram-Negative Bacteria:
Escherichia coli
Proteus mirabilis

Most isolates of indole positive Proteus (Proteus vulgaris), Enterobacter spp., Morganella morganii, Providencia rettgeri, Serratia spp., and Pseudomonas spp. are resistant to cefazolin.

Susceptibility Test Methods

For specific information regarding susceptibility test interpretive criteria and associated test methods and quality control standards recognized by FDA for this drug, please see: https://www.fda.gov/STIC.

INDICATIONS AND USAGE

Cefazolin for Injection, USP is indicated in the treatment of the following serious infections due to susceptible organisms:

Respiratory Tract Infections: Due to S. pneumoniae, Klebsiella species, H. influenzae, S. aureus (penicillin-sensitive and penicillin-resistant), and group A beta-hemolytic streptococci. Injectable benzathine penicillin is considered to be the drug of choice in treatment and prevention of streptococcal infections, including the prophylaxis of rheumatic fever.

Cefazolin for Injection is effective in the eradication of streptococci from the nasopharynx; however, data establishing the efficacy of Cefazolin for Injection in the subsequent prevention of rheumatic fever are not available at present.

Urinary Tract Infections: Due to E. coli, P. mirabilis, Klebsiella species, and some strains of enterobacter and enterococci.

Skin and Skin Structure Infections: Due to S. aureus (penicillin-sensitive and penicillin-resistant), group A beta-hemolytic streptococci, and other strains of streptococci.

Biliary Tract Infections: Due to E. coli, various strains of streptococci, P. mirabilis, Klebsiella species, and S. aureus.

Bone and Joint Infections: Due to S. aureus.

Genital Infections: (i.e., prostatitis, epididymitis) due to E. coli, P. mirabilis, Klebsiella species, and some strains of enterococci.

Septicemia: Due to S. pneumoniae, S. aureus (penicillin-sensitive and penicillin-resistant), P. mirabilis, E. coli and Klebsiella species.

Endocarditis: Due to S. aureus (penicillin-sensitive and penicillin-resistant) and group A beta-hemolytic streptococci.

Perioperative Prophylaxis: The prophylactic administration of Cefazolin for Injection preoperatively, intraoperatively and postoperatively may reduce the incidence of certain postoperative infections in patients undergoing surgical procedures which are classified as contaminated or potentially contaminated (e.g., vaginal hysterectomy, and cholecystectomy in high-risk patients such as those older than 70 years, with acute cholecystitis, obstructive jaundice, or common duct bile stones).

The perioperative use of Cefazolin for Injection may also be effective in surgical patients in whom infection at the operative site would present a serious risk (e.g., during open-heart surgery and prosthetic arthroplasty).

The prophylactic administration of Cefazolin for Injection should usually be discontinued within a 24 hour period after the surgical procedure. In surgery where the occurrence of infection may be particularly devastating (e.g., open-heart surgery and prosthetic arthroplasty), the prophylactic administration of Cefazolin for Injection may be continued for 3 to 5 days following the completion of surgery.

If there are signs of infection, specimens for cultures should be obtained for the identification of the causative organism so that appropriate therapy may be instituted (see DOSAGE AND ADMINISTRATION).

To reduce the development of drug-resistant bacteria and maintain the effectiveness of Cefazolin for Injection, USP and other antibacterial drugs, Cefazolin for Injection, USP should be used only to treat or prevent infections that are proven or strongly suspected to be caused by susceptible bacteria. When culture and susceptibility information are available, they should be considered in selecting or modifying antibacterial therapy. In the absence of such data, local epidemiology and susceptibility patterns may contribute to the empiric selection of therapy.

CONTRAINDICATIONS

Cefazolin for Injection IS CONTRAINDICATED IN PATIENTS WITH KNOWN ALLERGY TO THE CEPHALOSPORIN GROUP OF ANTIBIOTICS.

WARNINGS

BEFORE THERAPY WITH CEFAZOLIN FOR INJECTION IS INSTITUTED, CAREFUL INQUIRY SHOULD BE MADE TO DETERMINE WHETHER THE PATIENT HAS HAD PREVIOUS HYPERSENSITIVITY REACTIONS TO CEFAZOLIN, CEPHALOSPORINS, PENICILLINS, OR OTHER DRUGS. IF THIS PRODUCT IS GIVEN TO PENICILLIN-SENSITIVE PATIENTS, CAUTION SHOULD BE EXERCISED BECAUSE CROSS-HYPERSENSITIVITY AMONG BETA-LACTAM ANTIBIOTICS HAS BEEN CLEARLY DOCUMENTED AND MAY OCCUR IN UP TO 10% OF PATIENTS WITH A HISTORY OF PENICILLIN ALLERGY. IF AN ALLERGIC REACTION TO CEFAZOLIN FOR INJECTION OCCURS, DISCONTINUE TREATMENT WITH THE DRUG. SERIOUS ACUTE HYPERSENSITIVITY REACTIONS MAY REQUIRE TREATMENT WITH EPINEPHRINE AND OTHER EMERGENCY MEASURES, INCLUDING OXYGEN, IV FLUIDS, IV ANTIHISTAMINES, CORTICOSTEROIDS, PRESSOR AMINES, AND AIRWAY MANAGEMENT, AS CLINICALLY INDICATED.

Pseudomembranous colitis has been reported with nearly all antibacterial agents, including cefazolin, and may range in severity from mild to life-threatening. Therefore, it is important to consider this diagnosis in patients who present with diarrhea subsequent to the administration of antibacterial agents.

Treatment with antibacterial agents alters the normal flora of the colon and may permit overgrowth of clostridia. Studies indicate that a toxin produced by Clostridium difficile is a primary cause of “antibiotic-associated colitis”.

After the diagnosis of pseudomembranous colitis has been established, therapeutic measures should be initiated. Mild cases of pseudomembranous colitis usually respond to drug discontinuation alone. In moderate to severe cases, consideration should be given to management with fluids and electrolytes, protein supplementation, and treatment with an oral antibacterial drug clinically effective against C. difficile colitis.

PRECAUTIONS

General

Prolonged use of Cefazolin for Injection may result in the overgrowth of nonsusceptible organisms. Careful clinical observation of the patient is essential.

When Cefazolin for Injection is administered to patients with low urinary output because of impaired renal function, lower daily dosage is required (see DOSAGE AND ADMINISTRATION).

As with other β-lactam antibiotics, seizures may occur if inappropriately high doses are administered to patients with impaired renal function (see DOSAGE AND ADMINISTRATION).

Cefazolin for Injection, as with all cephalosporins, should be prescribed with caution in individuals with a history of gastrointestinal disease, particularly colitis.

Cephalosporins may be associated with a fall in prothrombin activity. Those at risk include patients with renal or hepatic impairment or poor nutritional state, as well as patients receiving a protracted course of antimicrobial therapy, and patients previously stabilized on anticoagulant therapy. Prothrombin time should be monitored in patients at risk and exogenous vitamin K administered as indicated.

Prescribing Cefazolin for Injection in the absence of a proven or strongly suspected bacterial infection or a prophylactic indication is unlikely to provide benefit to the patient and increases the risk of the development of drug-resistant bacteria.

Drug Interactions

Probenecid may decrease renal tubular secretion of cephalosporins when used concurrently, resulting in increased and more prolonged cephalosporin blood levels.

Drug/Laboratory Test Interactions

A false positive reaction for glucose in the urine may occur with Benedict's solution, Fehling’s solution or with CLINITEST® tablets, but not with enzyme-based tests such as CLINISTIX®.

Positive direct and indirect antiglobulin (Coombs) tests have occurred; these may also occur in neonates whose mothers received cephalosporins before delivery.

Information for Patients

Patients should be counseled that antibacterial drugs including Cefazolin for Injection, should only be used to treat bacterial infections. They do not treat viral infections (e.g., the common cold). When Cefazolin for Injection is prescribed to treat a bacterial infection, patients should be told that although it is common to feel better early in the course of therapy, the medication should be taken exactly as directed. Skipping doses or not completing the full course of therapy may: (1) decrease the effectiveness of the immediate treatment, and (2) increase the likelihood that bacteria will develop resistance and will not be treatable by Cefazolin for Injection or other antibacterial drugs in the future.

Carcinogenesis/Mutagenesis

Mutagenicity studies and long-term studies in animals to determine the carcinogenic potential of Cefazolin for Injection have not been performed.

Pregnancy

Teratogenic Effects

Reproduction studies have been performed in rats, mice and rabbits at doses up to 25 times the human dose and have revealed no evidence of impaired fertility or harm to the fetus due to Cefazolin for Injection. There are, however, no adequate and well-controlled studies in pregnant women. Because animal reproduction studies are not always predictive of human response, this drug should be used during pregnancy only if clearly needed.

Labor and Delivery

When cefazolin has been administered prior to caesarean section, drug levels in cord blood have been approximately one quarter to one third of maternal drug levels. The drug appears to have no adverse effect on the fetus.

Nursing Mothers

Cefazolin for Injection is present in very low concentrations in the milk of nursing mothers. Caution should be exercised when Cefazolin for Injection is administered to a nursing woman.

Pediatric Use

Safety and effectiveness for use in premature infants and neonates have not been established. See DOSAGE AND ADMINISTRATION for recommended dosage in pediatric patients older than 1 month.

Geriatric Use

Of the 920 subjects who received Cefazolin for Injection in clinical studies, 313 (34%) were 65 years and over, while 138 (15%) were 75 years and over. No overall differences in safety or effectiveness were observed between these subjects and younger subjects. Other reported clinical experience has not identified differences in responses between the elderly and younger patients, but greater sensitivity of some older individuals cannot be ruled out.

This drug is known to be substantially excreted by the kidney, and the risk of toxic reactions to this drug may be greater in patients with impaired renal function. Because elderly patients are more likely to have decreased renal function, care should be taken in dose selection, and it may be useful to monitor renal function (see PRECAUTIONS, General and DOSAGE AND ADMINISTRATION).

ADVERSE REACTIONS

The following reactions have been reported:

Gastrointestinal
Diarrhea, oral candidiasis (oral thrush), vomiting, nausea, stomach cramps, anorexia, and pseudomembranous colitis. Onset of pseudomembranous colitis symptoms may occur during or after antibiotic treatment (see WARNINGS). Nausea and vomiting have been reported rarely.

Allergic
Anaphylaxis, eosinophilia, itching, drug fever, skin rash, Stevens-Johnson syndrome.

Hematologic
Neutropenia, leukopenia, thrombocytopenia, thrombocythemia.

Hepatic
Transient rise in SGOT, SGPT, and alkaline phosphatase levels has been observed. As with other cephalosporins, reports of hepatitis have been received.

Renal
As with other cephalosporins, reports of increased BUN and creatinine levels, as well as renal failure, have been received.

Local Reactions
Rare instances of phlebitis have been reported at site of injection. Pain at the site of injection after intramuscular administration has occurred infrequently. Some induration has occurred.

Other Reactions
Genital and anal pruritus (including vulvar pruritus, genital moniliasis, and vaginitis).

To report SUSPECTED ADVERSE REACTIONS, contact Hikma Pharmaceuticals USA Inc. at 1-877-845-0689, or the FDA at 1-800-FDA-1088 or www.fda.gov/medwatch.

DOSAGE AND ADMINISTRATION

Usual Adult Dosage

Type of Infection | Dose | Dose Frequency
Moderate to severe infections | 500 mg to 1 gram | every 6 to 8 hours
Mild infections caused by susceptible gram–positive cocci | 250 mg to 500 mg | every 8 hours
Acute, uncomplicated urinary tract infections | 1 gram | every 12 hours
Pneumococcal pneumonia | 500 mg | every 12 hours
Severe, life-threatening infections (e.g., endocarditis, septicemia) [ln rare instances, doses of up to 12 grams of Cefazolin for Injection per day have been used.] | 1 gram to 1.5 grams | every 6 hours

Perioperative Prophylactic Use

To prevent postoperative infection in contaminated or potentially contaminated surgery, recommended doses are:

a. 1 gram IV or IM administered 1/2 hour to 1 hour prior to the start of surgery.

b. For lengthy operative procedures (e.g., 2 hours or more), 500 mg to 1 gram IV or IM during surgery (administration modified depending on the duration of the operative procedure).

c. 500 mg to 1 gram IV or IM every 6 to 8 hours for 24 hours postoperatively.

It is important that (1) the preoperative dose be given just (1/2 to 1 hour) prior to the start of surgery so that adequate antibiotic levels are present in the serum and tissues at the time of initial surgical incision; and (2) Cefazolin for Injection be administered, if necessary, at appropriate intervals during surgery to provide sufficient levels of the antibiotic at the anticipated moments of greatest exposure to infective organisms.

In surgery where the occurrence of infection may be particularly devastating (e.g., open-heart surgery and prosthetic arthroplasty), the prophylactic administration of Cefazolin for Injection may be continued for 3 to 5 days following the completion of surgery.

Dosage Adjustment for Patients with Reduced Renal Function

Cefazolin for Injection may be used in patients with reduced renal function with the following dosage adjustments: Patients with a creatinine clearance of 55 mL/min. or greater or a serum creatinine of 1.5 mg % or less can be given full doses. Patients with creatinine clearance rates of 35 to 54 mL/min. or serum creatinine of 1.6 to 3 mg % can also be given full doses but dosage should be restricted to at least 8 hour intervals. Patients with creatinine clearance rates of 11 to 34 mL/min. or serum creatinine of 3.1 to 4.5 mg % should be given 1/2 the usual dose every 12 hours. Patients with creatinine clearance rates of 10 mL/min. or less or serum creatinine of 4.6 mg % or greater should be given 1/2 the usual dose every 18 to 24 hours. All reduced dosage recommendations apply after an initial loading dose appropriate to the severity of the infection. Patients undergoing peritoneal dialysis: See CLINICAL PHARMACOLOGY.

Pediatric Dosage

In pediatric patients, a total daily dosage of 25 to 50 mg per kg (approximately 10 to 20 mg per pound) of body weight, divided into 3 or 4 equal doses, is effective for most mild to moderately severe infections. Total daily dosage may be increased to 100 mg per kg (45 mg per pound) of body weight for severe infections. Since safety for use in premature infants and in neonates has not been established, the use of Cefazolin for Injection in these patients is not recommended.

Pediatric Dosage Guide
Weight |  | 25 mg/kg/day Divided into 3 Doses |  | 25 mg/kg/day Divided into 4 Doses
Lbs | Kg | Approximate Single Dose mg/q8h | Vol. (mL) needed with dilution of 125 mg/mL | Approximate Single Dose mg/q6h | Vol. (mL) needed with dilution of 125 mg/mL
10 | 4.5 | 40 mg | 0.35 mL | 30 mg | 0.25 mL
20 | 9 | 75 mg | 0.6 mL | 55 mg | 0.45 mL
30 | 13.6 | 115 mg | 0.9 mL | 85 mg | 0.7 mL
40 | 18.1 | 150 mg | 1.2 mL | 115 mg | 0.9 mL
50 | 22.7 | 190 mg | 1.5 mL | 140 mg | 1.1 mL

Weight |  | 50 mg/kg/day Divided into 3 Doses |  | 50 mg/kg/day Divided into 4 Doses
Lbs | Kg | Approximate Single Dose mg/q8h | Vol. (mL) needed with dilution of 225 mg/mL | Approximate Single Dose mg/q6h | Vol. (mL) needed with dilution of 225 mg/mL
10 | 4.5 | 75 mg | 0.35 mL | 55 mg | 0.25 mL
20 | 9 | 150 mg | 0.7 mL | 110 mg | 0.5 mL
30 | 13.6 | 225 mg | 1 mL | 170 mg | 0.75 mL
40 | 18.1 | 300 mg | 1.35 mL | 225 mg | 1 mL
50 | 22.7 | 375 mg | 1.7 mL | 285 mg | 1.25 mL

In pediatric patients with mild to moderate renal impairment (creatinine clearance of 70 to 40 mL/min.), 60 percent of the normal daily dose given in equally divided doses every 12 hours should be sufficient. In patients with moderate impairment (creatinine clearance of 40 to 20 mL/min.), 25 percent of the normal daily dose given in equally divided doses every 12 hours should be adequate. Pediatric patients with severe renal impairment (creatinine clearance of 20 to 5 mL/min.) may be given 10 percent of the normal daily dose every 24 hours. All dosage recommendations apply after an initial loading dose.

RECONSTITUTION

Preparation of Parenteral Solution

Parenteral drug products should be SHAKEN WELL when reconstituted, and inspected visually for particulate matter prior to administration. If particulate matter is evident in reconstituted fluids, the drug solutions should be discarded.

When reconstituted or diluted according to the instructions below, Cefazolin for Injection is stable for 24 hours at room temperature or for 10 days if stored under refrigeration (5°C or 41°F). Reconstituted solutions may range in color from pale yellow to yellow without a change in potency.

Note on Refrigeration and Crystallization

Refrigeration of reconstituted solutions may result in crystal formation. This crystallization phenomenon is expected after refrigeration and does not affect the quality or potency of the
product. Before administration, reconstituted solutions with a crystallized appearance should be redissolved by hand-warming the vials until the solution is clear.

Single-Dose Vials

For IM injection, IV direct (bolus) injection or IV infusion, reconstitute with Sterile Water for Injection according to the following table. SHAKE WELL.

Vial Size | Amount of Diluent | Approximate Concentration | Approximate Available Volume
1 gram | 2.5 mL | 330 mg/mL | 3 mL

ADMINISTRATION

Intramuscular Administration

Reconstitute vials with Sterile Water for Injection according to the dilution table above. Shake well until dissolved. Cefazolin for Injection should be injected into a large muscle mass. Pain on injection is infrequent with Cefazolin for Injection.

Intravenous Administration

Direct (bolus) injection: Following reconstitution according to the above table, further dilute vials with approximately 5 mL Sterile Water for Injection. Inject the solution slowly over 3 to 5 minutes, directly or through tubing for patients receiving parenteral fluids (see list below).

Intermittent or continuous infusion: Dilute reconstituted Cefazolin for Injection in 50 to 100 mL of 1 of the following solutions:

- Sodium Chloride Injection, USP
- 5% or 10% Dextrose Injection, USP
- 5% Dextrose in Lactated Ringer's Injection, USP
- 5% Dextrose and 0.9% Sodium Chloride Injection, USP
- 5% Dextrose and 0.45% Sodium Chloride Injection, USP
- 5% Dextrose and 0.2% Sodium Chloride Injection, USP
- Lactated Ringer's Injection, USP
- Invert Sugar 5% or 10% in Sterile Water for Injection
- Ringer's Injection, USP
- 5% Sodium Bicarbonate Injection, USP

HOW SUPPLIED

Cefazolin for Injection, USP is supplied in vials containing cefazolin sodium equivalent to 1 gram cefazolin.

Cefazolin for Injection, USP | Vial Size | Packaged | NDC No.
1 gram | 10 mL | Carton of 25 vials | 72572-055-25

Also available as Pharmacy Bulk Package, as follows:

Cefazolin for Injection, USP | Vial Size | Packaged | NDC No.
10 grams | 100 mL | Carton of 10 vials | 72572-056-10

As with other cephalosporins, Cefazolin for Injection, USP tends to darken depending on storage conditions; within the stated recommendations, however, product potency is not adversely affected.

Before reconstitution protect from light and store at 20° to 25°C (68° to 77°F) [See USP Controlled Room Temperature].

CLINITEST is a registered trademark of Miles, Inc.
CLINISTIX is a registered trademark of Bayer Corporation.

Distributed by:
Civica, Inc.
Lehi, Utah 84048

Manufactured by:
Hikma Farmacêutica (Portugal), S.A.
Estrada do Rio da Mó, 8, 8A e 8B – Fervença – 2705-906 Terrugem SNT, Portugal

Revised: November 2025

PIN603-CIV/3

PRINCIPAL DISPLAY PANEL

NDC 72572-055-01 Rx Only
Cefazolin
for Injection, USP
1 gram* per vial
For Intravenous or Intramuscular use

NDC 72572-055-25 Rx Only
Cefazolin
for Injection, USP
1 gram* per vial
For Intravenous or Intramuscular use
25 x 1 g Vials